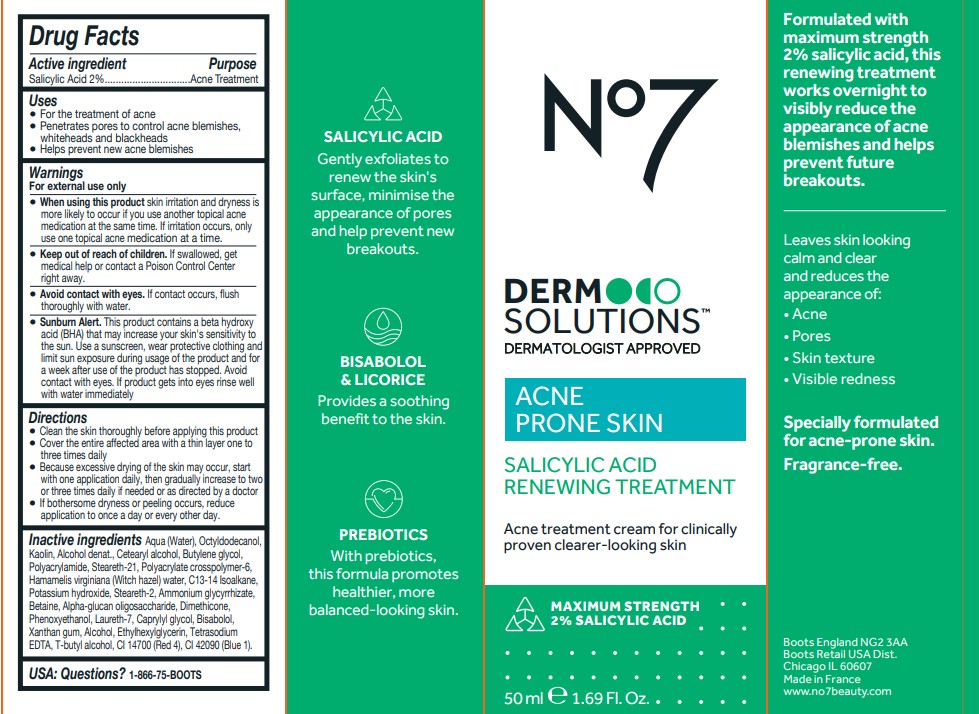 DRUG LABEL: Derm Solutions Salicylic Acid Treatment
NDC: 61589-9801 | Form: LOTION
Manufacturer: BCM Cosmetique SAS
Category: otc | Type: HUMAN OTC DRUG LABEL
Date: 20250914

ACTIVE INGREDIENTS: SALICYLIC ACID 1 g/1 g
INACTIVE INGREDIENTS: ETHYLHEXYLGLYCERIN; OCTYLDODECANOL; WATER; KAOLIN; PHENOXYETHANOL; POLYACRYLATE CROSSPOLYMER-6; STEARETH-2; LAURETH-7; T-BUTYL ALCOHOL; DIMETHICONE; CAPRYLYL GLYCOL; FD&C RED NO. 4; AMMONIUM GLYCYRRHIZATE; C13-14 ISOPARAFFIN; HAMAMELIS VIRGINIANA TOP WATER; STEARETH-21; ALPHA-GLUCAN OLIGOSACCHARIDE; CETEARYL ALCOHOL; BUTYLENE GLYCOL; BETAINE; TETRASODIUM EDTA; ALCOHOL; POLYACRYLAMIDE (CROSSLINKED; 2 MOLE PERCENT BISACRYLAMIDE); POTASSIUM HYDROXIDE; BISABOLOL; FD&C BLUE NO. 1; XANTHAN GUM

Derm Solutions Salicyclic Acid Renewing Treatment

Inactive Ingredients

Aqua (Water), Octyldodecanol,
Kaolin, Alcohol denat., Cetearyl alcohol, Butylene glycol,
Polyacrylamide, Steareth-21, Polyacrylate crosspolymer-6,
Hamamelis virginiana (Witch hazel) water, C13-14 Isoalkane,
Potassium hydroxide, Steareth-2, Ammonium glycyrrhizate,
Betaine, Alpha-glucan oligosaccharide, Dimethicone,
Phenoxyethanol, Laureth-7, Caprylyl glycol, Bisabolol,
Xanthan gum, Alcohol, Ethylhexylglycerin, Tetrasodium
EDTA, T-butyl alcohol, CI 14700 (Red 4), CI 42090 (Blue 1).

DIRECTIONS - USAGE

● For the treatment of acne
● Penetrates pores to control acne blemishes,
whiteheads and blackheads
● Helps prevent new acne blemishes

DIRECTIONS

Directions ● Clean the skin thoroughly before applying this product ● Cover the entire affected area with a thin layer one to three times daily ● Because excessive drying of the skin may occur, start with one application daily, then gradually increase to two or three times daily if needed or as directed by a doctor ● If bothersome dryness or peeling occurs, reduce application to once a day or every other day.

KEEP OUT OF REACH OF CHILDREN

For external use only ● When using this product skin irritation and dryness is more likely to occur if you use another topical acne medication at the same time. If irritation occurs, only use one topical acne medication at a time. ● Keep out of reach of children. If swallowed, get medical help or contact a Poison Control Center right away. ● Avoid contact with eyes. If contact occurs, flush thoroughly with water. ● Sunburn Alert. This product contains a beta hydroxy acid (BHA) that may increase your skin's sensitivity to the sun. Use a sunscreen, wear protective clothing and limit sun exposure during usage of the product and for a week after use of the product has stopped. Avoid contact with eyes. If product gets into eyes rinse well with water immediatel

USES

For the treatment of acne ● Penetrates pores to control acne blemishes, whiteheads and blackheads ● Helps prevent new acne blemishes

Uses

. For the treatment of acne
. Penetrates pores to control acne blemishes,
whiteheads and blackheads
. Helps prevent new acne blemishes

Warnings